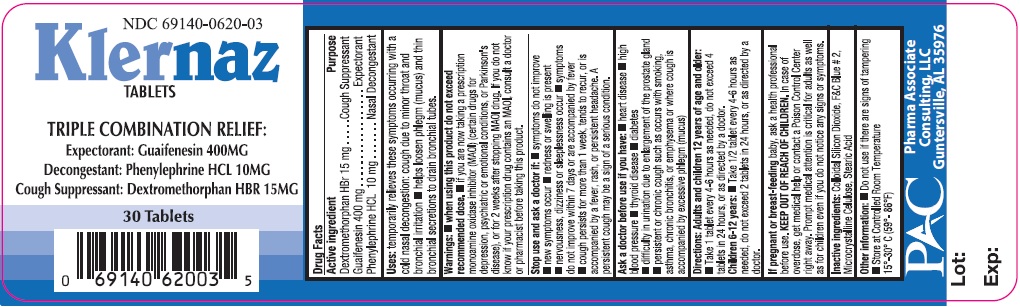 DRUG LABEL: Klernaz
NDC: 69140-620 | Form: TABLET
Manufacturer: Pharma Associate Consultants, Inc
Category: otc | Type: HUMAN OTC DRUG LABEL
Date: 20150807

ACTIVE INGREDIENTS: DEXTROMETHORPHAN HYDROBROMIDE 15 mg/1 1; GUAIFENESIN 400 mg/1 1; PHENYLEPHRINE HYDROCHLORIDE 10 mg/1 1
INACTIVE INGREDIENTS: COLLOIDAL SILICON DIOXIDE; CELLULOSE, MICROCRYSTALLINE; STEARIC ACID

Klernaz Tablets

Drug Facts

Active ingredient

Dextromethorphan HBr 15 mg

Guaifenesin 400 mg

Phenylephrine HCL 10 mg

Purpose

Cough Suppressant

Expectorant

Nasal Decongestant

INDICATIONS AND USAGE

Uses: temporarily relieves these symptoms occurring with a cold nasal decongestion: cough due to minor throat and bronchial irritation

- helps loosen phlegm (mucus) and thin bronchial secretions to drain bronchial tubes.

Warnings:

- when using this product do not exceed recommended dose.
- if you are now taking a prescription monoamine oxidase inhibitor (MAOI) (certain drugs for depression, psychiatric or emotional conditions, or Parkinson's disease), or for 2 weeks after stopping MAOI drug. If you do not know if your prescription drug contains an MAOI, consult a doctor or pharmacist before taking this product.

Stop use and ask a doctor if:

- symptoms do not improve
- new symptoms occur
- redness or swelling is present
- nervousness, dizziness or sleeplessness occur
- symptoms do not improve within 7 days or are accompanied by fever
- cough persists for more than 1 week, tends to recur, or is accompanied by a fever, rash, or persistent headache. A persistent cough may be a sign of a serious condition.

Ask a doctor before use if you have

- heart disease
- high blood pressure
- thyroid disease
- diabetes
- difficulty in urination due to enlargement of the prostate gland
- persistent or chronic cough such as occurs with smoking, asthma, chronic bronchitis, or emphysema or where cough is accompanied by excessive phlegm (mucus)

Directions:

Adults and children 12 years of age and older

- Take 1 tablet every 4-6 hours as needed, do not exceed 4 tablets in 24 hours, or as directed by a doctor.

Children 6-12 years:

- Take 1/2 tablet every 4-6 hours as needed, do not exceet 2 tablets in 24 hours, or as directed by a doctor.

PREGNANCY OR BREAST FEEDING

If pregnant or breast-feeding baby, ask a health professional before use.

KEEP OUT OF REACH OF CHILDREN.

In case of overdose, get medical help or contact a Poison Control Center right away. Prompt medical attention is critical for adults as well as children even if you do not notice any signs or symptoms.

INACTIVE INGREDIENT

Colloidal Silicon Dioxide, F&C Blue # 2, Microcrystalline Cellulose, Stearic Acid

Other information:

- Do not use if there are signs of tampering
- Store at Controlled Room Temperature 15°-30°C (59°-86°F)

PAC

Pharma Associate

Consulting, LLC

Guntersville, AL 35976

Principal Display Panel - 30 Tablets Bottle Labeling

NDC 69140-0620-03

Klernaz

TABLETS

TRIPLE COMBINATION RELIEF:

Expectorant: Guaifenesin 400MG

Decongestant: Phenylephrine HCL 10MG

Cough Suppressant: Dextromethorphan HBR 15MG

30 Tablets